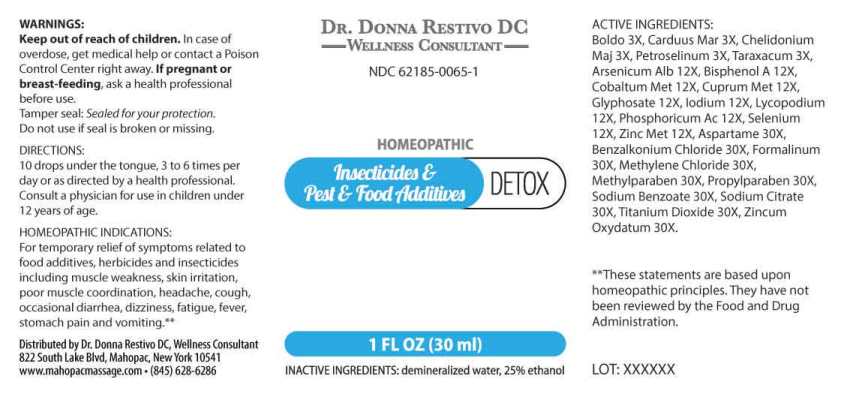 DRUG LABEL: Insecticides/Pest/Food Additives Detox
NDC: 62185-0065 | Form: LIQUID
Manufacturer: Dr. Donna Restivo DC
Category: homeopathic | Type: HUMAN OTC DRUG LABEL
Date: 20250523

ACTIVE INGREDIENTS: PEUMUS BOLDUS LEAF 3 [hp_X]/1 mL; MILK THISTLE 3 [hp_X]/1 mL; CHELIDONIUM MAJUS WHOLE 3 [hp_X]/1 mL; PETROSELINUM CRISPUM WHOLE 3 [hp_X]/1 mL; TARAXACUM OFFICINALE 3 [hp_X]/1 mL; ARSENIC TRIOXIDE 12 [hp_X]/1 mL; BISPHENOL A 12 [hp_X]/1 mL; COBALT 12 [hp_X]/1 mL; COPPER 12 [hp_X]/1 mL; GLYPHOSATE 12 [hp_X]/1 mL; IODINE 12 [hp_X]/1 mL; LYCOPODIUM CLAVATUM SPORE 12 [hp_X]/1 mL; PHOSPHORIC ACID 12 [hp_X]/1 mL; SELENIUM 12 [hp_X]/1 mL; ZINC 12 [hp_X]/1 mL; ASPARTAME 30 [hp_X]/1 mL; BENZALKONIUM CHLORIDE 30 [hp_X]/1 mL; FORMALDEHYDE SOLUTION 30 [hp_X]/1 mL; METHYLENE CHLORIDE 30 [hp_X]/1 mL; METHYLPARABEN 30 [hp_X]/1 mL; PROPYLPARABEN 30 [hp_X]/1 mL; SODIUM BENZOATE 30 [hp_X]/1 mL; SODIUM CITRATE, UNSPECIFIED FORM 30 [hp_X]/1 mL; TITANIUM DIOXIDE 30 [hp_X]/1 mL; ZINC OXIDE 30 [hp_X]/1 mL
INACTIVE INGREDIENTS: WATER; ALCOHOL

DRUG FACTS:

ACTIVE INGREDIENTS:

Boldo 3X, Carduus Marianus 3X, Chelidonium Majus 3X, Petroselinum Sativum 3X, Taraxacum Officinale 3X, Arsenicum Album 12X, Bisphenol A 12X, Cobaltum Metallicum 12X, Cuprum Metallicum 12X, Glyphosate 12X, Iodium 12X, Lycopodium Clavatum 12X, Phosphoricum Acidum 12X, Selenium Metallicum 12X, Zincum Metallicum 12X, Aspartame 30X, Benzalkonium Chloride 30X, Formalinum 30X, Methylene Chloride 30X, Methyl Paraben 30X, Propyl Paraben 30X, Sodium Benzoate 30X, Sodium Citrate 30X, Titanium Dioxide 30X, Zincum Oxydatum 30X.

HOMEOPATHIC INDICATIONS:

For temporary relief of symptoms related to food additives, herbicides and insecticides including muscle weakness, skin irritation, poor muscle coordination, headache, cough, occasional diarrhea, dizziness, fatigue, fever, stomach pain and vomiting.**

**These statements are based upon homeopathic principles. They have not been reviewed by the Food and Drug Administration.

WARNINGS:

Keep out of reach of children. In case of overdose, get medical help or contact a Poison Control Center right away.

If pregnant or breast-feeding, ask a health professional before use.

Tamper seal: Sealed for Your Protection. Do not use if seal is broken or missing.

Keep out of reach of children. In case of overdose, get medical help or contact a Poison Control Center right away.

DIRECTIONS:

10 drops under the tongue, 3 to 6 times per day or as directed by a health professional. Consult a physician for use in children under 12 years of age.

HOMEOPATHIC INDICATIONS:

For temporary relief of symptoms related to food additives, herbicides and insecticides including muscle weakness, skin irritation, poor muscle coordination, headache, cough, occasional diarrhea, dizziness, fatigue, fever, stomach pain and vomiting.**

**These statements are based upon homeopathic principles. They have not been reviewed by the Food and Drug Administration.

INACTIVE INGREDIENTS:

demineralized water, 25% ethanol

QUESTIONS:

Distributed by Dr. Donna Restivo DC, Wellness Consultant

822 South Lake Blvd, Mahopac, New York 10541

www.mahopacmassage.com • (845) 628-6286

PACKAGE LABEL DISPLAY:

Dr. Donna Restivo DC
Wellness Consultant

NDC 62185-0065-1

HOMEOPATHIC
Insecticides & Pest & Food Additives DETOX

1 FL OZ (30 ml)